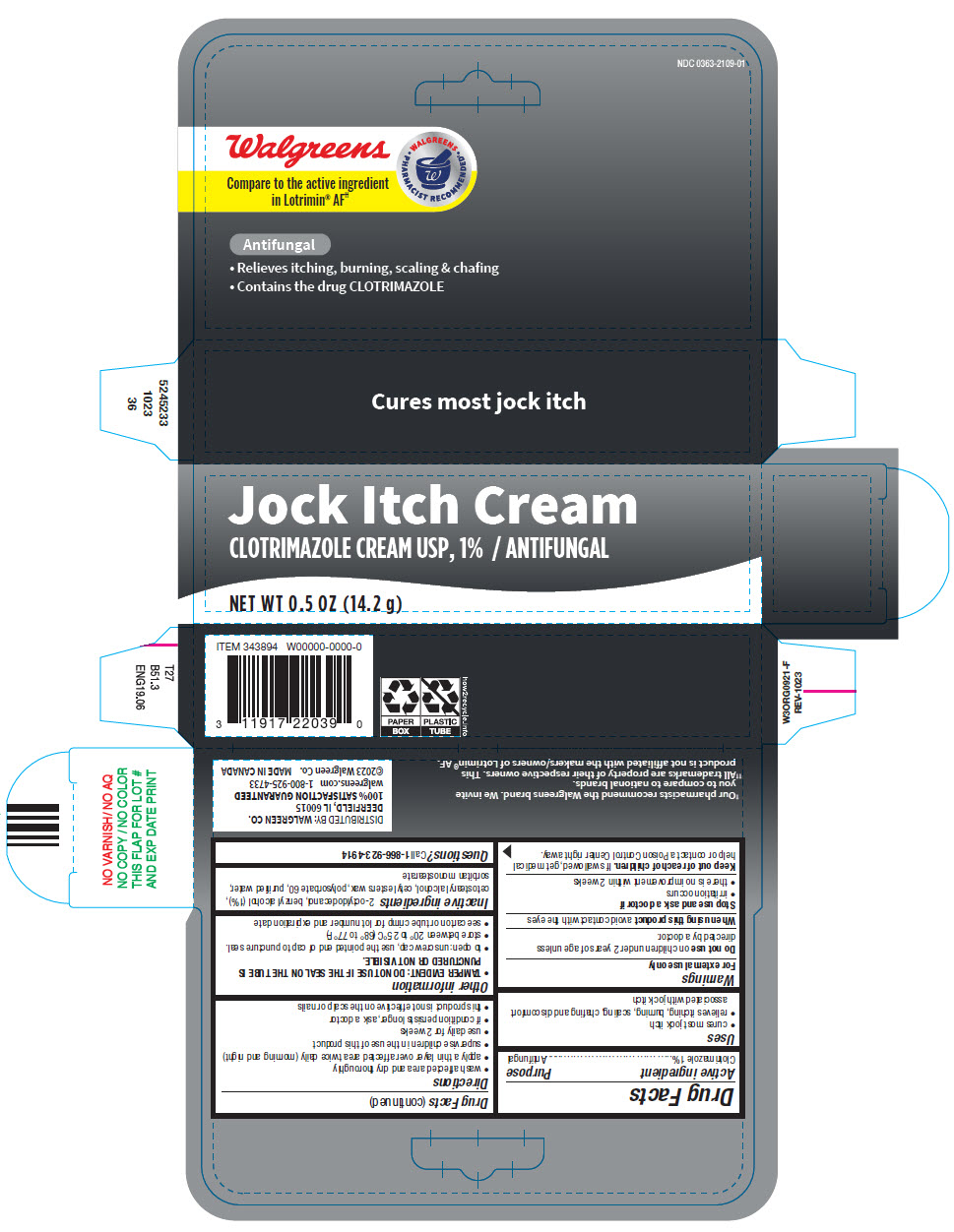 DRUG LABEL: Walgreens 

NDC: 0363-2109 | Form: CREAM
Manufacturer: Walgreen Company
Category: otc | Type: HUMAN OTC DRUG LABEL
Date: 20250711

ACTIVE INGREDIENTS: CLOTRIMAZOLE 10 mg/1 g
INACTIVE INGREDIENTS: BENZYL ALCOHOL; CETOSTEARYL ALCOHOL; CETYL ESTERS WAX; OCTYLDODECANOL; POLYSORBATE 60; WATER; SORBITAN MONOSTEARATE

Walgreens
Jock Itch Cream

Drug Facts

Active ingredient

Clotrimazole 1%

Purpose

Antifungal

Uses

- cures most jock itch
- relieves itching, burning, scaling, chafing and discomfort associated with jock itch

Warnings

For external use only

Do not useon children under 2 years of age unless directed by a doctor.

When using this productavoid contact with the eyes

Stop use and ask a doctor if

- irritation occurs
- there is no improvement within 2 weeks

Keep out of reach of children.If swallowed, get medical help or contact a Poison Control Center right away.

Directions

- wash affected area and dry thoroughly
- apply a thin layer over affected area twice daily (morning and night)
- supervise children in the use of this product
- use daily for 2 weeks
- if condition persists longer, ask a doctor
- this product is not effective on the scalp or nails

Other information

- TAMPER EVIDENT: DO NOT USE IF THE SEAL ON THE TUBE IS PUNCTURED OR NOT VISIBLE
- to open: unscrew cap, use the pointed end of cap to puncture seal.
- store between 20° to 25°C (68° to 77°F)
- see carton or tube crimp for lot number and expiration date

Inactive ingredients

2-octyldodecanol, benzyl alcohol (1%), cetostearyl alcohol, cetyl esters wax, polysorbate 60, purified water, sorbitan monostearate

Questions?

Call 1-866-923-4914

DISTRIBUTED BY:
WALGREEN CO.
200 WILMOT RD.,
DEERFIELD, IL 60015

PRINCIPAL DISPLAY PANEL - 14.2 g Tube Carton

Jock Itch Cream

CLOTRIMAZOLE CREAM USP, 1% / ANTIFUNGAL

NET WT 0.5 OZ (14.2 g)